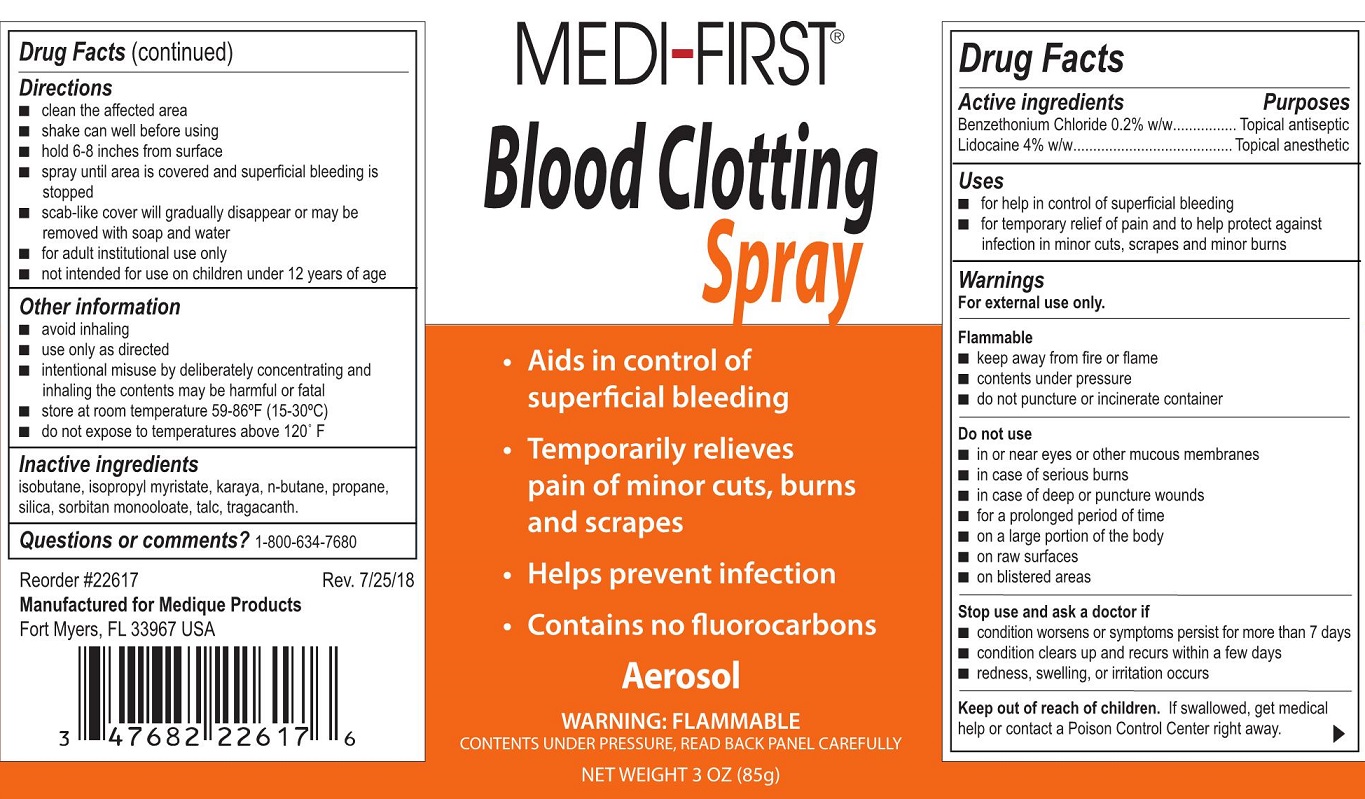 DRUG LABEL: Blood Clotting First Aid
NDC: 47682-226 | Form: AEROSOL, SPRAY
Manufacturer: Unifirst First Aid Corporation
Category: otc | Type: HUMAN OTC DRUG LABEL
Date: 20250908

ACTIVE INGREDIENTS: LIDOCAINE 3400 mg/85 g; BENZETHONIUM CHLORIDE 170 mg/85 g
INACTIVE INGREDIENTS: ISOBUTANE; ISOPROPYL MYRISTATE; KARAYA GUM; BUTANE; PROPANE; SILICON DIOXIDE; SORBITAN MONOOLEATE; TALC; TRAGACANTH

Medi-First Blood Clotting Spray

Active Ingredients

Benzethonium Chloride 0.2% w/w
Lidocaine 4% w/w

Purpose

Topical antiseptic
Topical anesthetic

Uses

- for help in control of superficial bleeding

- for temporary relief of pain and to help protect against infection in minor cuts, scrapes, and burns

Warnings

For external use only

Flammable

- keep away from fire or flame

- contents under pressure

- do not puncture or incinerate container

Do not use

- in or near eyes or other mucus membranes
- in case of serious burns
- in case of deep or puncture wounds
- for a prolonged period of time
- on a large portion of the body
- on raw surfaces
- on blistered areas

Stop use and ask a doctor if

- condition worsens or symptoms persist for more than 7 days
- condition clears up and recurs within a few days
- redness, swelling, or irritation occurs

Keep out of reach of children. .

If swallowed, get medical help or contact a Poison Control Center right away

Directions

- clean the affected area
- shake can well before using
- hold 6-8 inches from surface
- spray until area is covered and superficial bleeding is stopped
- scab-like cover will gradually disappear or may be removed with soap and water
- for adult institutional use only
- not intended for use on children under 12 years of age

Other information

- avoid inhaling
- use only as directed
- intentional misuse by deliberately concentrating and inhaling the contents may be harmful or fatal
- Store at room temperature 59-86°F (15-30°C)
- do not expose to temperatures above 120°F

Inactive ingredients

isobutane, isopropyl myristate, karaya, n-butane, propane, silica, sorbitan monooloate, talc, tragacanth.

Questions or comments?

1-800-634-7680

Medi-First Blood Clotting Spray Label

Medi-First® Blood Clotting Spray

- Aids in control of bleeding
- Temporarily relieves pain of minor cuts, burns and scrapes
- Helps prevent infection
- Coantains no fluorocarbons
- Aerosol
- Warning: FLAMMABLE
- Contents under pressure, read Back Panel Carefully
- Net Weight 3 oz (85g)